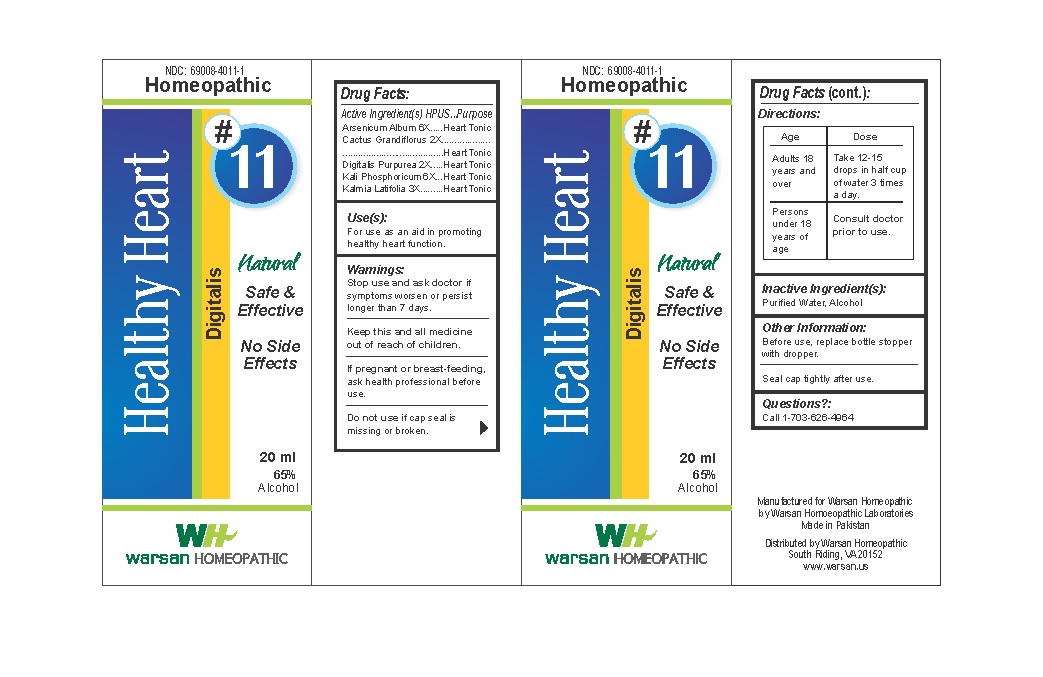 DRUG LABEL: Combination Remedy 11 - Healthy Heart
NDC: 69008-4011 | Form: SOLUTION/ DROPS
Manufacturer: Warsan Homoeopathic Laboratories
Category: homeopathic | Type: HUMAN OTC DRUG LABEL
Date: 20171225

ACTIVE INGREDIENTS: DIGITALIS 2 [hp_X]/1 mL; POTASSIUM PHOSPHATE, DIBASIC 6 [hp_X]/1 mL; ARSENIC TRIOXIDE 6 [hp_X]/1 mL; SELENICEREUS GRANDIFLORUS STEM 2 [hp_X]/1 mL; KALMIA LATIFOLIA LEAF 6 [hp_X]/1 mL
INACTIVE INGREDIENTS: ALCOHOL; WATER

Stop use and ask doctor if symptoms worsen or persist longer than 7 days.

If pregnant or breast-feeding, ask health professional before use.

Do not use if tamper evident seal is missing or broken.

Keep out of reach of children.

ACTIVE INGREDIENT

Arsenicum Album 6X

Cactus Grandiflorus 2X

Digitalis Purpurea 2X

Kali Phosphoricum 6X

Kalmia Latifolia 3X

PURPOSE

For use as an aid in promoting healthy heart function.

INACTIVE INGREDIENT

Purified Water

Alcohol

DOSAGE AND ADMINISTRATION

Adults 18 years and older: Take 10-15 drops in half cup of water 3 times a day.

Not intended for use by persons under 18 years.

INDICATIONS AND USAGE

For use as an aid in promoting healthy heart function.